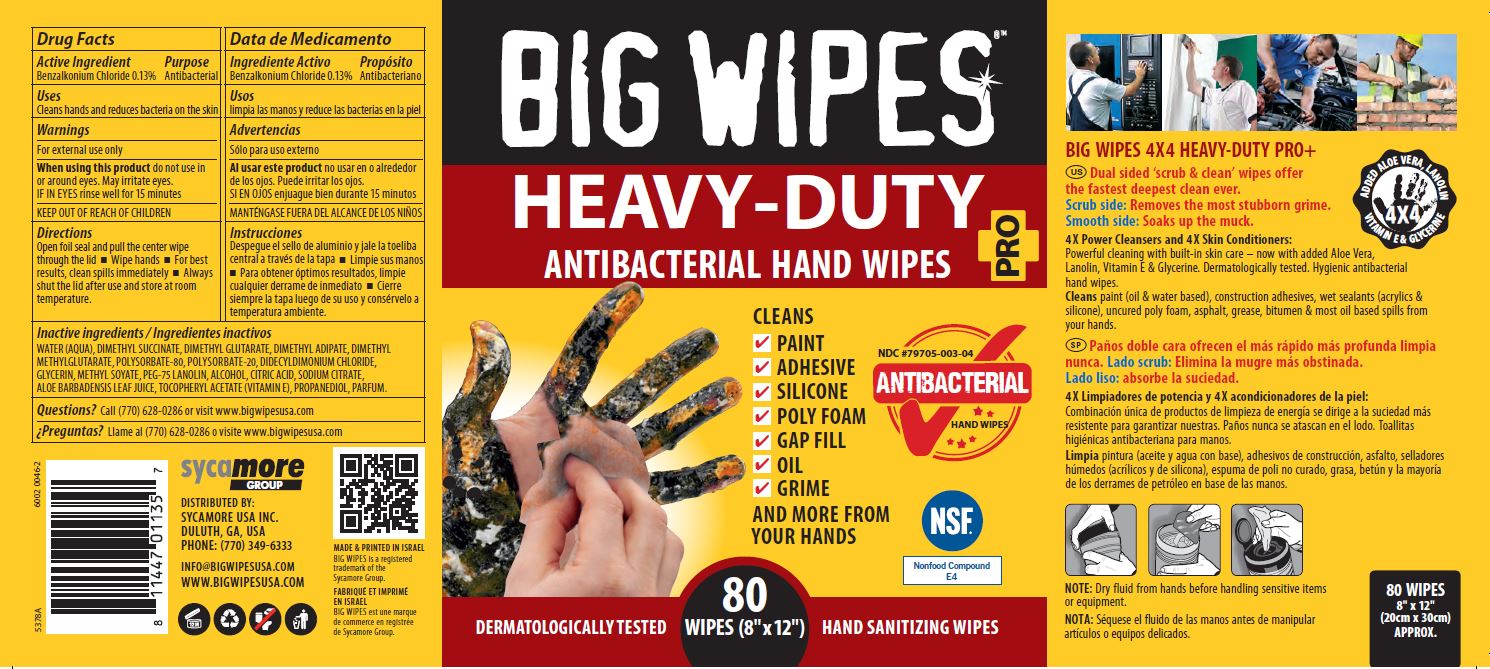 DRUG LABEL: BIG WIPES Heavy Duty
NDC: 79705-003 | Form: CLOTH
Manufacturer: Sycamore USA Inc.
Category: otc | Type: HUMAN OTC DRUG LABEL
Date: 20221123

ACTIVE INGREDIENTS: BENZALKONIUM CHLORIDE 1.3 mg/1 mL
INACTIVE INGREDIENTS: ALOE VERA LEAF; GLYCERIN; PROPANEDIOL; WATER; METHYL SOYATE; PEG-75 LANOLIN; DIMETHYL ADIPATE; DIMETHYL METHYLGLUTARATE; CITRIC ACID MONOHYDRATE; ALCOHOL; SODIUM CITRATE; .ALPHA.-TOCOPHEROL ACETATE; DIMETHYL SUCCINATE; DIMETHYL GLUTARATE; POLYSORBATE 80; POLYSORBATE 20; DIDECYLDIMONIUM CHLORIDE

BIG WIPES
Heavy-Duty

Active Ingredient

Benzalkonium Chloride 0.13%

Purpose

Antibacterial

Uses

Cleans hands and reduce bacteria on the skin

Warnings

For external use only

When using this product do not use in or around eyes. May irritate eyes.

IF IN EYES rinse well for 15 minutes

Directions

Open foil seal and pull the center wipe through the lid

- Wipe hands
- For best results, clean spills immediately
- Always shut the lid after use and store at room temperature.

Inactive ingredients

WATER (AQUA), DIMETHYL SUCCINATE, DIMETHYL GLUTARATE, DIMETHYL ADIPATE, DIMETHYL METYLGLUTARATE, POLYSORBATE-80, POLYSORBATE-20, DIDECYLDIMONIUM CHLORIDE, GLYCERIN, METHYL SOYATE, PEG-75 LANOLIN, ALCOHOL, CITRIC ACID, SODIUM CITRATE, ALOE BARBADENSIS LEAF JUICE, TOCOPHERYL ACETATE (VITAMIN E), PROPANEDIOL, PARFUM.

Questions?

Call (770) 628-0286 or visit www.bigwipesusa.com

PACKAGE LABEL

BIG WIPES

HEAVY-DUTY

ANTIBACTERIAL HAND WIPES

PRO+

CLEANS

PAINT

ADHESIVE

SILICONE

PLY FOAM

GAP FILL

OIL

GRIME

and MORE

FROM YOUR HANDS

NDC #79705-003-04

ANTIBACTERIAL

Hand Wipes

NSF

Nonfood Compound

E4

DERMATOLOGICALLY TESTED

80

WIPES (8" x 12")

HAND SANITIZING WIPES